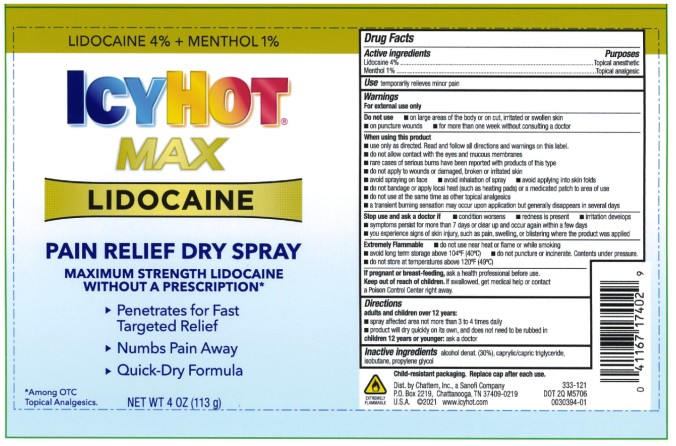 DRUG LABEL: Icy Hot Lidocaine Dry
NDC: 41167-1740 | Form: SPRAY
Manufacturer: Chattem, Inc.
Category: otc | Type: HUMAN OTC DRUG LABEL
Date: 20260115

ACTIVE INGREDIENTS: LIDOCAINE 4 g/100 mL; MENTHOL 1 g/100 mL
INACTIVE INGREDIENTS: ALCOHOL; MEDIUM-CHAIN TRIGLYCERIDES; ISOBUTANE; PROPYLENE GLYCOL

Icy Hot Lidocaine Dry Spray

ICY HOT LIDOCAINE DRY SPRAY

Drug Facts

Active ingredients

Lidocaine 4%

Menthol 1%

Purposes

Topical anesthetic

Topical analgesic

Use

temporarily relieves minor pain

Warnings

For external use only

Do not use

■ on large areas of the body or on cut, irritated or swollen skin

■ on puncture wounds

■ for more than one week without consulting a doctor

When using this product

■ use only as directed. Read and follow all directions and warnings on this label.

■ do not allow contact with the eyes and mucous membranes

■ rare cases of serious burns have been reported with products of this type

■ do not apply to wounds or damaged, broken or irritated skin

■ avoid spraying on face

■ avoid inhalation of spray

■ do not bandage or apply local heat (such as heating pads) or a medicated patch to area of use

■ do not use at the same time as other topical analgesics

■ a transient burning sensation may occur upon application but generally disappears in several days

■ avoid applying into skin folds

Stop use and ask a doctor if

■ condition worsens

■ redness is present

■ irritation develops

■ symptoms persist for more than 7 days or clear up and occur again within a few days

■ you experience signs of skin injury, such as pain, swelling, or blistering where the product was applied

Extremely Flammable

■ do not use near heat or flame or while smoking

■ avoid long term storage above 104°F (40°C)

■ do not puncture or incinerate. Contents under pressure.

■ do not store at temperatures above 120°F (49°C)

If pregnant or breast-feeding,

ask a health professional before use.

Keep out of reach of children.

If swallowed, get medical help or contact a Poison Control Center right away.

Directions

adults and children over 12 years:

■ spray affected not more than 3 to 4 daily

■ product will dry quickly on its own, and does not need to be rubbed in

children 12 years or younger: ask a doctor

Inactive ingredients:

alcohol denat. (30%), caprylic/capric triglyceride, isobutane, propylene glycol

PRINCIPAL DISPLAY PANEL

LIDOCAINE 4% + MENTHOL 1%
ICY HOT
MAX
LIDOCAINE
PAIN RELIEF DRY SPRAY
NET WT 4 OZ (113 g)